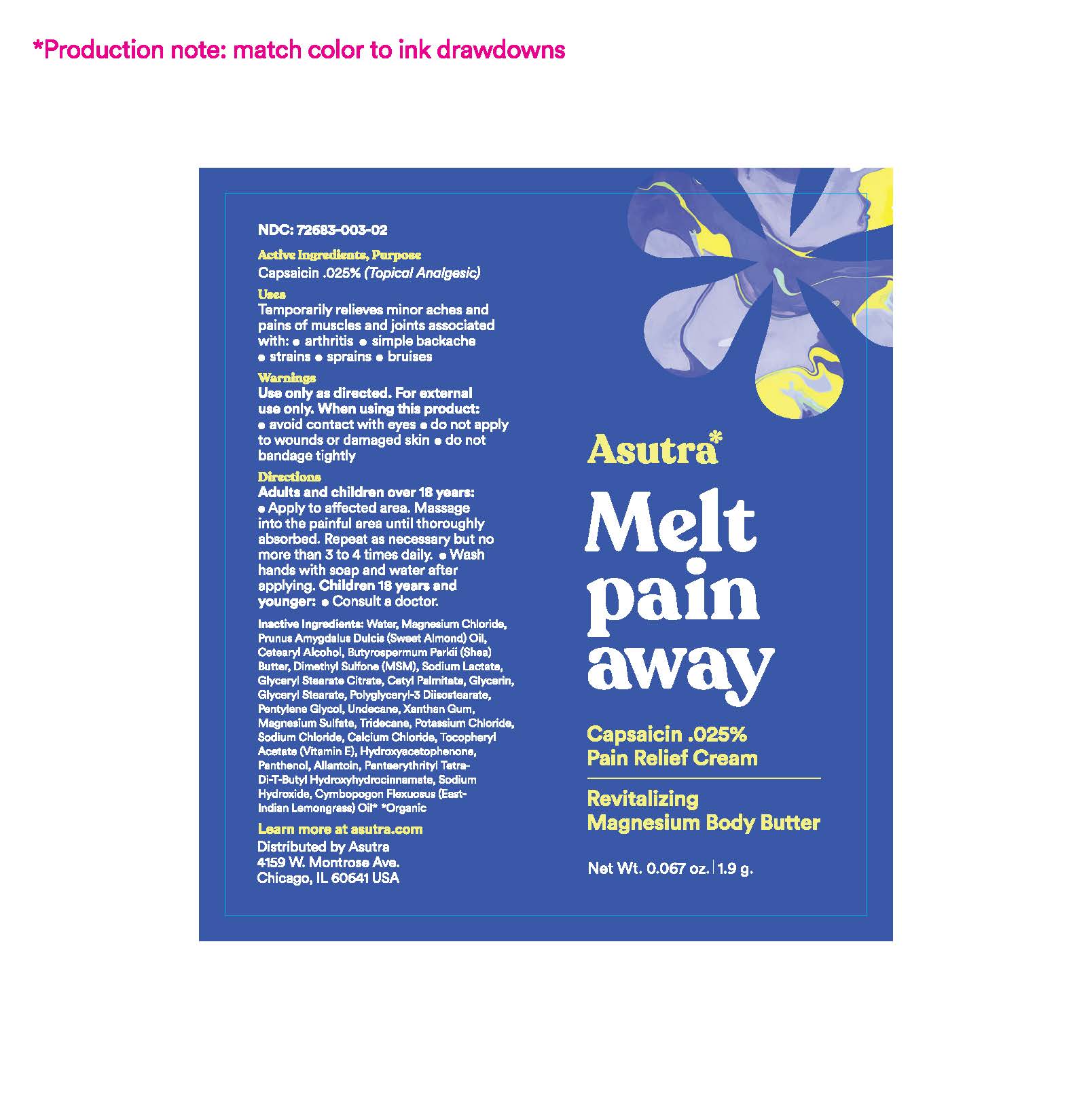 DRUG LABEL: Melt Pain Away
NDC: 72683-003 | Form: CREAM
Manufacturer: Proximity Capital Partners LLC dba Asutra
Category: otc | Type: HUMAN OTC DRUG LABEL
Date: 20250618

ACTIVE INGREDIENTS: CAPSAICIN 0.025 g/100 g
INACTIVE INGREDIENTS: CETOSTEARYL ALCOHOL; SODIUM LACTATE; CETYL PALMITATE; POLYGLYCERYL-3 DISTEARATE; MAGNESIUM SULFATE, UNSPECIFIED; HYDROXYACETOPHENONE; PANTHENOL; SODIUM HYDROXIDE; CYMBOPOGON FLEXUOSUS LEAF; PENTAERYTHRITOL TETRAKIS(3-(3,5-DI-TERT-BUTYL-4-HYDROXYPHENYL)PROPIONATE); MAGNESIUM CHLORIDE; SHEA BUTTER; DIMETHYL SULFONE; GLYCERYL STEARATE CITRATE; GLYCERIN; GLYCERYL STEARATE SE; UNDECANE; XANTHAN GUM; TRIDECANE; POTASSIUM CHLORIDE; CALCIUM CHLORIDE; .ALPHA.-TOCOPHEROL ACETATE; ALMOND OIL; PENTYLENE GLYCOL; SODIUM CHLORIDE; ALLANTOIN; WATER

Melt Pain Away (Asutra)

ACTIVE INGREDIENT

Capsaicin .025%

PURPOSE

Topical Analgesic

INDICATIONS AND USAGE

Temporarily relieves minor aches and pains of muscles and joints associated with:

- arthritis
- simple backache
- strains
- sprains
- bruises

WARNINGS

Use only as directed.

For external use only.

When using this product:

- avoid contact with eyes
- do not apply to wounds or damaged skin
- do not bandage tightly

Stop use and ask doctor if:

- condition worsens
- symptoms persist for more than 7 days, or clear up and reoccur again with a few days
- redness is present
- irritation develops.

PREGNANCY OR BREAST FEEDING

If pregnant or breastfeeding,ask a health professional before use.

Keep out of reach of children. If accidentally ingested, get medical help or contact Poison Control Center immediately.

DOSAGE AND ADMINISTRATION

Adults and children over 18 years:

- Apply to affected area. Massage into the painful area until thoroughly absorbed. Repeat as necessary but no more than 3 to 4

times daily.

- Wash hands with soap and water after applying.

Children 18 years and younger:

- Consult a doctor.

STORAGE AND HANDLING

- Store in a cool, dry place.
- Keep away from excessive heat or flame.
- Tamper-evident for your protection. Use only if safety seal is intact

INACTIVE INGREDIENT

Water, Magnesium Chloride, Prunus Amygdalus Dulcis (Sweet Almond) Oil, Cetearyl Alcohol, Butyrospermum Parkii (Shea) Butter, Dimethyl Sulfone (MSM), Sodium Lactate, Glyceryl Stearate Citrate, Cetyl Palmitate, Glycerin, Glyceryl Stearate, Polyglyceryl-3 Diisostearate, Pentylene Glycol, Undecane, Xanthan Gum, Magnesium Sulfate, Tridecane, Potassium Chloride, Sodium Chloride, Calcium Chloride, Tocopheryl Acetate (Vitamin E), Hydroxyacetophenone, Panthenol, Allantoin, Pentaerythrityl Tetra-Di-T-Butyl Hydroxyhydrocinnamate, Sodium Hydroxide, Cymbopogon Flexuosus (East-Indian Lemongrass) Oil* *Organic

QUESTIONS

888-819-6472; Monday–Friday, 9am–5pm CT
Report any serious side effects to number above.